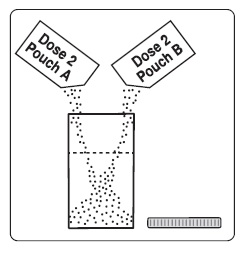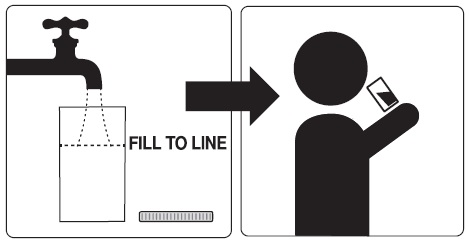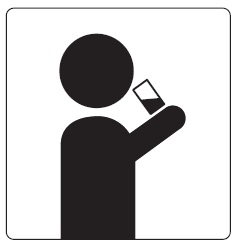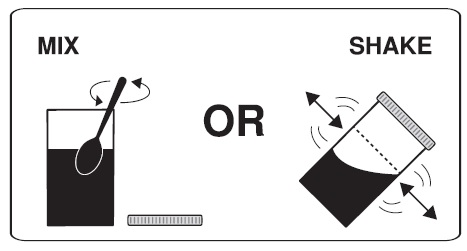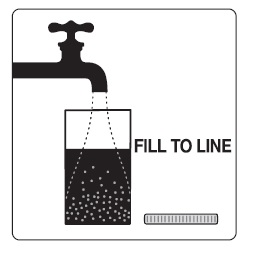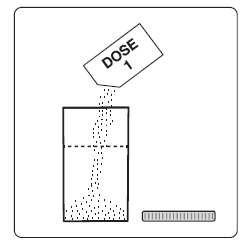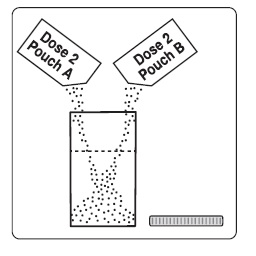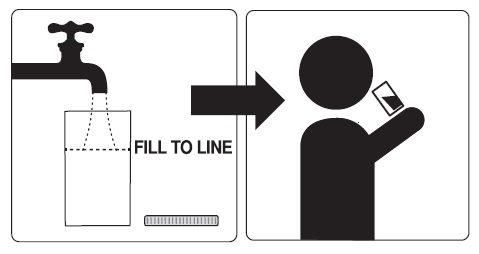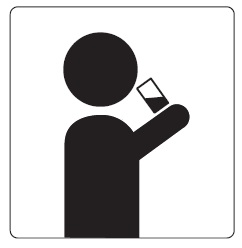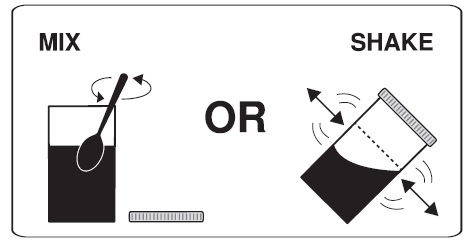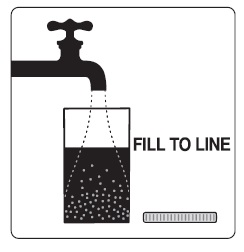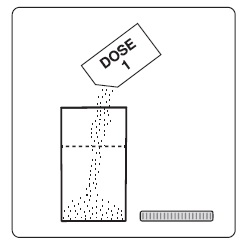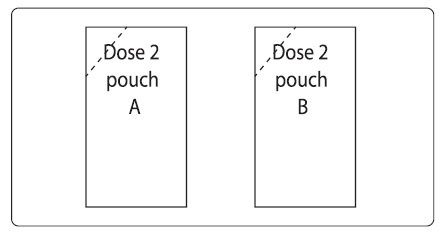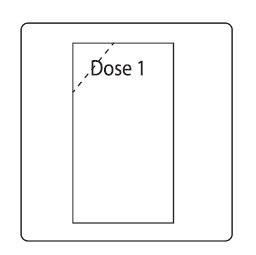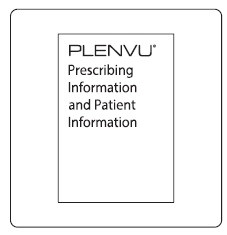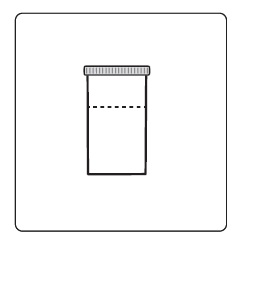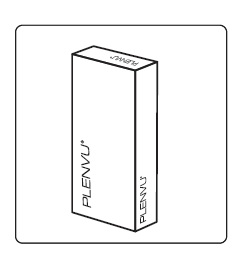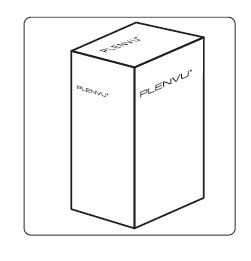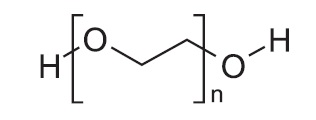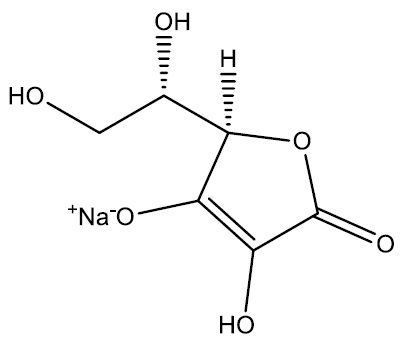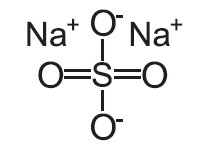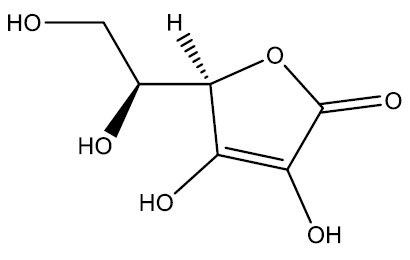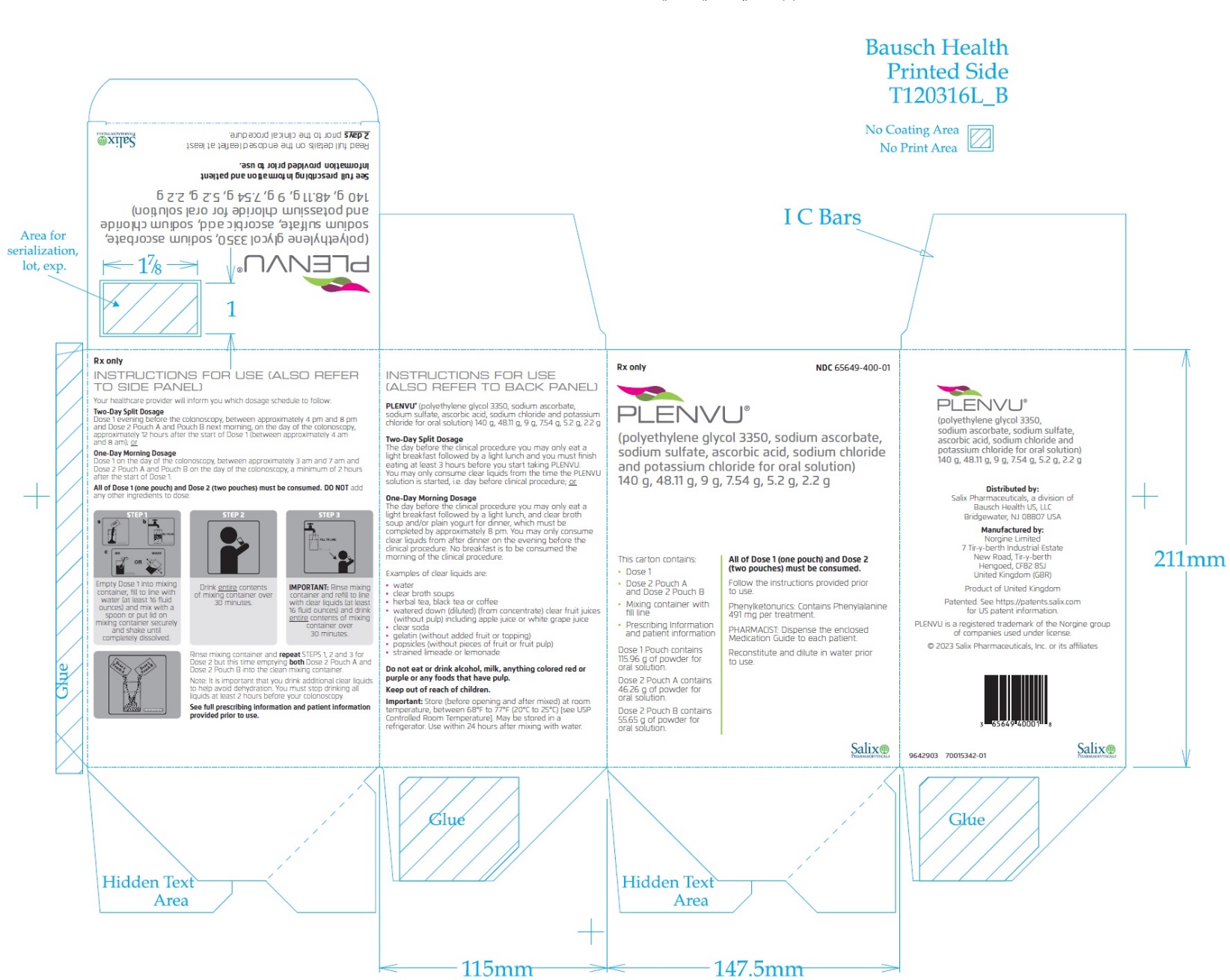 DRUG LABEL: Plenvu
NDC: 65649-400 | Form: KIT | Route: ORAL
Manufacturer: Salix Pharmaceuticals, Inc
Category: prescription | Type: HUMAN PRESCRIPTION DRUG LABEL
Date: 20230901

ACTIVE INGREDIENTS: POLYETHYLENE GLYCOL 3350 100 g/1 1; SODIUM SULFATE 9 g/1 1; SODIUM CHLORIDE 2 g/1 1; POTASSIUM CHLORIDE 1 g/1 1; POLYETHYLENE GLYCOL 3350 40 g/1 1; SODIUM CHLORIDE 3.2 g/1 1; POTASSIUM CHLORIDE 1.2 g/1 1; SODIUM ASCORBATE 48.11 g/1 1; ASCORBIC ACID 7.54 g/1 1
INACTIVE INGREDIENTS: SUCRALOSE; CITRIC ACID MONOHYDRATE; MANGO; ASPARTAME

HIGHLIGHTS OF PRESCRIBING INFORMATION

These highlights do not include all the information needed to use PLENVU safely and effectively. See full prescribing information for PLENVU.
PLENVU® (polyethylene glycol 3350, sodium ascorbate, sodium sulfate,
ascorbic acid, sodium chloride and potassium chloride for oral solution)
Initial U.S. Approval: 2006

RECENT MAJOR CHANGES

Dosage and Administration (2.1) 9/2023

1 INDICATIONS AND USAGE

PLENVU is an osmotic laxative indicated for cleansing of the colon in preparation for colonoscopy in adults. (1)

2 DOSAGE AND ADMINISTRATION

Preparation and Administration:

- Two doses of PLENVU are required for a complete preparation for colonoscopy, using a “Two-Day” or “One-Day” dosage regimen. (2.1)
- Reconstitute PLENVU in water prior to ingestion. (2.1)
- Consume additional clear liquids after each dose of PLENVU in both dosing regimens. (2.1, 5.1)
- Administer oral medications at least 1 hour before starting each dose of PLENVU. (2.1, 7.2)

Recommended Dosage Regimens:

- Two-Day Split Dosage: Dose 1 the evening before the colonoscopy (approximately 4 pm to 8 pm) and Dose 2 the next morning (approximately12 hours after the start of Dose 1). (2.1, 2.2)
- One-Day Morning Dosage: Dose 1 the morning of the colonoscopy (approximately 3 am to 7 am) and Dose 2 a minimum of 2 hours after the start of Dose 1. (2.1, 2.3)
- For complete information on dosing, preparation and administration, see full prescribing information. (2.1, 2.2, 2.3)

3 DOSAGE FORMS AND STRENGTHS

For Oral Solution: First dose: one pouch labeled Dose 1; Second dose: two pouches labeled Dose 2 Pouch A and Dose 2 Pouch B.

- Dose 1 contains 100 grams of polyethylene glycol (PEG) 3350, 9 grams of sodium sulfate, 2 grams of sodium chloride, and 1 gram of potassium chloride. (3)
- Dose 2 Pouch A contains 40 grams of PEG 3350, 3.2 grams of sodium chloride, and 1.2 grams of potassium chloride. (3)
- Dose 2 Pouch B contains 48.11 grams of sodium ascorbate and 7.54 grams of ascorbic acid. (3)

4 CONTRAINDICATIONS

- Gastrointestinal (GI) obstruction (4, 5.6)
- Bowel perforation (4, 5.6)
- Gastric retention (4)
- Ileus (4)
- Toxic megacolon (4)
- Hypersensitivity to any ingredient in PLENVU (4, 5.10)

5 WARNINGS AND PRECAUTIONS

- Risk of fluid and electrolyte abnormalities: Encourage adequate hydration, assess concurrent medications, and consider laboratory assessments prior to and after use. (5.1, 5.2, 7.1)
- Cardiac arrhythmias: Consider pre-dose and post-colonoscopy ECGs in patients at increased risk. (5.2)
- Seizures: Use caution in patients with a history of seizures and patients at increased risk of seizure, including medications that lower the seizure threshold. (5.3, 7.1)
- Patients with renal impairment or taking concomitant medications that affect renal function: Use caution, ensure adequate hydration and consider testing. (5.4, 7.1, 8.6)
- Mucosal ulcerations: Consider potential for mucosal ulcerations when interpreting colonoscopy findings in patients with known or suspected inflammatory bowel disease. (5.5)
- Suspected GI obstruction or perforation: Rule out diagnosis before administration. (4, 5.6)
- Patients at risk for aspiration: Observe during administration. (5.7)
- Glucose-6-phosphate dehydrogenase deficiency (G6PD): Use with caution. (5.8)
- Risks in patients with phenylketonuria: Contains phenylalanine. (5.9)
- Hypersensitivity reactions, including anaphylaxis: Inform patients to seek immediate medical care if symptoms occur. (5.10)

6 ADVERSE REACTIONS

Most common adverse reactions (>2%) are nausea, vomiting, dehydration and abdominal pain/discomfort. (6.1)

To report SUSPECTED ADVERSE REACTIONS, contact Salix Pharmaceuticals at 1-800-321-4576 or FDA at 1-800-FDA-1088 or www.fda.gov/medwatch.

7 DRUG INTERACTIONS

Drugs that increase risks due to fluid and electrolyte changes. (7.1)

FULL PRESCRIBING INFORMATION

1 INDICATIONS AND USAGE

PLENVU® is indicated for cleansing of the colon in preparation for colonoscopy in adults.

2 DOSAGE AND ADMINISTRATION

2.1 Important Preparation and Administration Instructions

- Correct fluid and electrolyte abnormalities before treatment with PLENVU [see Warnings and Precautions (5.1)].
- Two doses of PLENVU are required for a complete preparation for colonoscopy. The time interval between the two doses depends on the regimen prescribed and the planned timing of the colonoscopy procedure [see Dosage and Administration (2.2, 2.3)].
- The recommended “Two-Day Split Dosage” method consists of two separate doses: the first dose is taken the evening before the colonoscopy and the second dose is taken the next day, the morning of the day of the colonoscopy [see Dosage and Administration (2.2)].
- The recommended “One-Day Morning Dosage” method consists of two separate doses: both doses are taken in the morning of the day of the colonoscopy, with a minimum of 2 hours between the start of the first dose and the start of the second dose [see Dosage and Administration (2.3)].
- Reconstitute each pouch of PLENVU in the mixing container with water prior to ingestion. It may take 2 to 3 minutes for complete dissolution. Do not reconstitute with other liquids and/or add starch-based thickeners to the mixing container [see Warnings and Precautions (5.7)].
- Consume additional clear liquids (including water) in both dosing regimens [see Dosage and Administration (2.2, 2.3), Warnings and Precautions (5.1)].
- Consume only clear liquids (no solid food) from the start of PLENVU treatment until after the colonoscopy.
- Do not eat or drink alcohol, milk, anything colored red or purple or any other foods containing pulp material.
- Do not take other laxatives while taking PLENVU.
- Administer oral medications at least 1 hour before starting each dose of PLENVU [see Drug Interactions (7.2)].
- Ensure completion of Dose 2, including all additional liquids, at least 2 hours before the colonoscopy.

2.2 Recommended Two-Day Split Dosage Regimen

The recommended Two-Day Split Dosage regimen commences in the evening of the day before the colonoscopy.

Instruct adult patients that on the day before the clinical procedure, they can consume a light breakfast followed by a light lunch, which must be completed at least 3 hours prior to the start of the first PLENVU dose.

Instruct patients to take two separate doses in conjunction with clear liquids as follows:

Dose 1 – In the evening before the colonoscopy, between approximately 4 pm and 8 pm:

1. Empty the contents of Dose 1 into the mixing container that comes with PLENVU.
2. Add water to the fill line on the mixing container (at least 16 fluid ounces). Do not add other ingredients to the PLENVU solution.
3. Thoroughly mix with a spoon or shake with lid on securely until completely dissolved (which may take 2 to 3 minutes).
4. Drink over the next 30 minutes. Be sure to drink all of the solution.
5. Refill the mixing container to the fill line (at least 16 fluid ounces) with clear liquids and drink over the next 30 minutes.
6. Consume additional clear liquids during the evening.
7. If severe bloating, abdominal distention, or abdominal pain occurs following the first dose, delay the second dose until the symptoms resolve.

Dose 2 – The next morning, on the day of the colonoscopy, approximately 12 hours after the start of Dose 1 (between approximately 4 am and 8 am):

1. Empty the contents of Dose 2 Pouch A and Dose 2 Pouch B into the mixing container that comes with PLENVU.
2. Add water to the fill line on the mixing container (at least 16 fluid ounces). Do not add other ingredients to the PLENVU solution.
3. Thoroughly mix with a spoon or shake with lid on securely until completely dissolved (which may take 2 to 3 minutes). Drink over the next 30 minutes. Be sure to drink all of the solution.
4. Refill the mixing container to the fill line (at least 16 fluid ounces) with clear liquids and drink over the next 30 minutes.
5. Consume additional water or clear liquids up to 2 hours before the colonoscopy or as prescribed by your doctor. Then stop drinking liquids until after the colonoscopy.

Stop drinking PLENVU temporarily or drink each portion at longer intervals if severe bloating, abdominal discomfort or distention occurs, until these symptoms resolve.

2.3 Recommended One-Day Morning Dosage Regimen

The recommended One-Day Morning Dosage regimen commences in the morning of the day of the colonoscopy.

Instruct adult patients that on the day before the clinical procedure, they can consume a light breakfast followed by a light lunch, and clear broth soup and/or plain yogurt for dinner, which should be completed by approximately 8 pm.

Instruct patients to take two separate doses in conjunction with clear liquids as follows:

Dose 1 – On the day of the colonoscopy, between approximately 3 am and 7 am:

1. Empty the contents of Dose 1 into the mixing container that comes with PLENVU.
2. Add water to the fill line on the mixing container (at least 16 fluid ounces). Do not add other ingredients to the PLENVU solution.
3. Thoroughly mix with a spoon or shake with lid on securely until completely dissolved (which may take 2 to 3 minutes).
4. Drink over the next 30 minutes. Be sure to drink all of the solution.
5. Refill the mixing container to the fill line (at least 16 fluid ounces) with clear liquids and drink over the next 30 minutes.
6. If severe bloating, abdominal distention, or abdominal pain occurs following the first dose, delay the second dose until the symptoms resolve.

Dose 2 – On the day of the colonoscopy, a minimum of 2 hours after the start of Dose 1:

1. Empty the contents of Dose 2 Pouch A and Dose 2 Pouch B into the mixing container that comes with PLENVU.
2. Add water to the fill line on the mixing container (at least 16 fluid ounces). Do not add other ingredients to the PLENVU solution.
3. Thoroughly mix with a spoon or shake with lid on securely until completely dissolved (which may take 2 to 3 minutes). Drink over the next 30 minutes. Be sure to drink all of the solution.
4. Refill the mixing container to the fill line (at least 16 fluid ounces) with clear liquids and drink over the next 30 minutes.
5. Consume additional water or clear liquids up to 2 hours before the colonoscopy or as prescribed by your doctor. Then stop drinking liquids until after the colonoscopy.

Stop drinking PLENVU temporarily or drink each portion at longer intervals if severe bloating, abdominal discomfort or distention occurs, until these symptoms resolve.

Storage:
After reconstitution, keep PLENVU solution at room temperature, between 68°F to 77°F (20°C to 25°C) [see USP Controlled Room Temperature]. The solution may also be stored in a refrigerator. Use within 24 hours after it is mixed in water.

3 DOSAGE FORMS AND STRENGTHS

PLENVU (polyethylene glycol 3350, sodium ascorbate, sodium sulfate, ascorbic acid, sodium chloride and potassium chloride for oral solution) is supplied as a white to yellow powder for reconstitution.

First dose: one pouch labeled Dose 1; Second dose: two pouches labeled Dose 2 Pouch A and Dose 2 Pouch B.

- Dose 1 contains 100 grams of polyethylene glycol (PEG) 3350, 9 grams of sodium sulfate, 2 grams of sodium chloride, and 1 gram of potassium chloride.
- Dose 2 Pouch A contains 40 grams of PEG 3350, 3.2 grams of sodium chloride, and 1.2 grams of potassium chloride.
- Dose 2 Pouch B contains 48.11 grams of sodium ascorbate and 7.54 grams of ascorbic acid.

4 CONTRAINDICATIONS

PLENVU is contraindicated in the following conditions:

- Gastrointestinal (GI) obstruction [see Warnings and Precautions (5.6)]
- Bowel perforation [see Warnings and Precautions (5.6)]
- Gastric retention
- Ileus
- Toxic megacolon
- Hypersensitivity to any ingredient in PLENVU [see Warnings and Precautions (5.10)]

5 WARNINGS AND PRECAUTIONS

5.1 Serious Fluid and Electrolyte Abnormalities

Advise patients to hydrate adequately before, during, and after the use of PLENVU. If a patient develops significant vomiting or signs of dehydration after taking PLENVU, consider performing post-colonoscopy laboratory tests (electrolytes, creatinine, and BUN).

Bowel preparations can cause fluid and electrolyte disturbances, which can lead to serious adverse reactions including cardiac arrhythmias, seizures, and renal impairment. Correct fluid and electrolyte abnormalities before treatment with PLENVU. PLENVU should be used with caution in patients using concomitant medications that increase the risk of electrolyte abnormalities [such as diuretics, angiotensin converting enzyme (ACE) inhibitors or angiotensin receptor blockers (ARBs)] [see Drug Interactions (7.1)]. Consider performing pre-dose and post-colonoscopy laboratory tests (sodium, potassium, calcium, creatinine, and BUN) in patients receiving these concomitant medications.

5.2 Cardiac Arrhythmias

There have been rare reports of serious arrhythmias (including atrial fibrillation) associated with the use of ionic osmotic laxative products for bowel preparation. These occur predominantly in patients with underlying cardiac risk factors and electrolyte disturbances. Use caution when prescribing PLENVU for patients at increased risk of arrhythmias (e.g., patients with a history of prolonged QT, uncontrolled arrhythmias, recent myocardial infarction, unstable angina, congestive heart failure, cardiomyopathy or electrolyte imbalance). Consider pre-dose and post-colonoscopy ECGs in patients at increased risk of serious cardiac arrhythmias.

5.3 Seizures

There have been rare reports of generalized tonic-clonic seizures and/or loss of consciousness associated with use of bowel preparation products in patients with no prior history of seizures. The seizure cases were associated with electrolyte abnormalities (e.g., hyponatremia, hypokalemia, hypocalcemia, and hypomagnesemia) and low serum osmolality. The neurologic abnormalities resolved with correction of fluid and electrolyte abnormalities.

Use caution when prescribing PLENVU for patients with a history of seizures and in patients at increased risk of seizure, such as patients taking medications that lower the seizure threshold (e.g., tricyclic antidepressants), patients withdrawing from alcohol or benzodiazepines, or patients with known or suspected hyponatremia. [see Drug Interactions (7.1)].

5.4 Use in Patients with Renal Impairment

Use PLENVU with caution in patients with renal impairment or patients taking concomitant medications that affect renal function (such as diuretics, ACE inhibitors, angiotensin receptor blockers, or nonsteroidal anti-inflammatory drugs) [see Drug Interactions (7.1)]. These patients may be at risk for renal injury. Advise these patients of the importance of adequate hydration before, during and after the use of PLENVU, and consider performing pre-dose and post-colonoscopy laboratory tests (electrolytes, creatinine, and BUN) in these patients [see Use in Specific Populations (8.6)].

5.5 Colonic Mucosal Ulceration, Ischemic Colitis and Ulcerative Colitis

Osmotic laxatives may produce colonic mucosal aphthous ulcerations, and there have been reports of more serious cases of ischemic colitis requiring hospitalization. Concurrent use of stimulant laxatives and PLENVU may increase the risk and is not recommended. Consider the potential for mucosal ulcerations resulting from the bowel preparation when interpreting colonoscopy findings in patients with known or suspected inflammatory bowel disease.

5.6 Use in Patients with Significant Gastrointestinal Disease

If gastrointestinal obstruction or perforation is suspected, perform appropriate diagnostic studies to rule out these conditions before administering PLENVU [see Contraindications (4)]. Use with caution in patients with severe ulcerative colitis.

5.7 Aspiration

Patients with impaired gag reflex or other swallowing abnormalities are at risk for regurgitation or aspiration of PLENVU. Observe these patients during the administration of PLENVU. Use with caution in these patients.

Do not combine PLENVU with starch-based thickeners [see Dosage and Administration (2.1)]. Polyethylene glycol (PEG), a component of PLENVU, when mixed with starch-thickened liquids reduces the viscosity of the starch-thickened liquid. When a PEG-based product used for another indication was mixed in starch-based pre-thickened liquids used in patients with dysphagia, thinning of the liquid occurred and cases of choking and potential aspiration were reported.

5.8 Glucose-6-Phosphate Dehydrogenase (G6PD) Deficiency

Since PLENVU contains sodium ascorbate and ascorbic acid, PLENVU should be used with caution in patients with glucose-6-phosphate dehydrogenase (G6PD) deficiency, especially G6PD deficiency patients with an active infection, with a history of hemolysis, or taking concomitant medications known to precipitate hemolytic reactions.

5.9 Risks in Patients with Phenylketonuria

Phenylalanine can be harmful to patients with phenylketonuria (PKU). PLENVU contains phenylalanine, a component of aspartame. Each PLENVU treatment contains 491 mg of phenylalanine. Before prescribing PLENVU to a patient with PKU, consider the combined daily amount of phenylalanine from all sources, including PLENVU.

5.10 Hypersensitivity Reactions

PLENVU contains PEG and may cause serious hypersensitivity reactions including anaphylaxis, angioedema, rash, urticaria, and pruritus [see Adverse Reactions (6.1, 6.2)]. Inform patients of the signs and symptoms of anaphylaxis, and instruct them to seek immediate medical care should signs and symptoms occur.

6 ADVERSE REACTIONS

The following serious or otherwise important adverse reactions for bowel preparations are described elsewhere in the labeling:

- Serious Fluid and Electrolyte Abnormalities [see Warnings and Precautions (5.1)]
- Cardiac Arrhythmias [see Warnings and Precautions (5.2)]
- Seizures [see Warnings and Precautions (5.3)]
- Patients with Renal Impairment [see Warnings and Precautions (5.4)]
- Colonic Mucosal Ulceration, Ischemic Colitis and Ulcerative Colitis [see Warnings and Precautions (5.5)]
- Patients with Significant Gastrointestinal Disease [see Warnings and Precautions (5.6)]
- Aspiration [see Warnings and Precautions (5.7)]
- Glucose-6-Phosphate Dehydrogenase (G6PD) Deficiency [see Warnings and Precautions (5.8)]
- Risks in Patients with Phenylketonuria [see Warnings and Precautions (5.9)]
- Hypersensitivity Reactions [see Warnings and Precautions (5.10)]

6.1 Clinical Trials Experience

Because clinical trials are conducted under widely varying conditions, adverse reaction rates observed in the clinical trials of a drug cannot be directly compared to rates in the clinical trials of another drug and may not reflect the rates observed in practice.

The safety of PLENVU Two-Day Split Dosage and One-Day Morning Dosage regimens was evaluated in two randomized, parallel group, multicenter, investigator-blinded clinical trials (Two-Day Split Dosage in the NOCT and MORA trials and One-Day Morning Dosage in the MORA trial) in 1351 adult patients undergoing colonoscopy. The mean age of the study population was 56 years (range 18 to 86 years), 92% of patients were Caucasian and 51% were female. In the NOCT trial, 61% of patients had mild renal impairment. In the MORA trial, 67% had mild renal impairment and 5% had moderate renal impairment. Patients with severe renal impairment were not enrolled in the clinical trials of PLENVU [see Clinical Studies (14)].

The most common adverse reactions (>2%) in the PLENVU treatment groups in both trials were: nausea, vomiting, dehydration and abdominal pain/discomfort.

Table 1 and Table 2 display adverse reactions reported in at least 1% of patients in one or more treatment group(s) in the NOCT and MORA trials, respectively. Since diarrhea was considered as a part of the efficacy assessment, it was not defined as an adverse reaction in these trials.

Table 1: Common Adverse Reactions* in Patients Undergoing Colonoscopy in the NOCT Trial by Treatment Group
Preferred Term | PLENVU Two-Day Split Dosage Regimen (N = 275) % | Trisulfate [Trisulfate: Two 6-ounce bottles of oral solution each containing sodium sulfate 17.5 grams, potassium sulfate 3.13 grams, magnesium sulfate 1.6 grams] Two-Day Split Dosage Regimen (N = 271) %
Nausea | 7 | 2
Vomiting | 6 | 3
Dehydration [Includes signs and symptoms of dehydration, including dizziness, dry mouth, orthostatic hypotension, pre-syncope, syncope, and thirst] | 4 | 2
Abdominal Pain/Discomfort [Includes abdominal discomfort, abdominal pain, lower abdominal pain, upper abdominal pain, and abdominal tenderness] | 2 | 2
Decline in Glomerular Filtration Rate (GFR) [Decreased or abnormal GFR] | 2 | 2
Electrolyte Abnormalities [Includes increased anion gap, decreased blood bicarbonate, hypomagnesemia, hyperosmolarity, hypokalemia, hyperkalemia, hypercalcemia, hypernatremia, hyperosmolar state, hyperuricemia, hypocalcemia, and hypophosphatemia] | 2 | 1
Fatigue | 2 | 1
Headache | 2 | 1
Abdominal Distension | 1 | 1
Gastritis | 1 | 1
Hiatus Hernia | 1 | 0
Nasopharyngitis | 1 | 1
* Reported in at least 1% of patients in either treatment group
N = Total number of patients in the treatment group

Table 2: Common Adverse Reactions* in Patients Undergoing Colonoscopy in the MORA Trial by Treatment Group
Preferred Term | PLENVU; One-Day Morning; Dosage Regimen; (N = 271); % | PLENVU; Two-Day Split; Dosage Regimen; (N = 265); % | 2 Liter PEG +; Electrolytes; Two-Day Split; Dosage Regimen [2 Liter PEG Plus Electrolytes: Two doses each containing PEG 3350 100 grams, sodium sulfate 7.5 grams, sodium chloride 2.691 grams, potassium chloride 1.015 grams, sodium ascorbate 5.9 grams, and ascorbic acid 4.7 grams]; (N = 269); %
Vomiting | 7 | 4 | 1
Nausea | 6 | 6 | 3
Dehydration [Includes signs and symptoms of dehydration, including dizziness, dry mouth, orthostatic hypotension, pre-syncope, syncope, and thirst] | 4 | 3 | 2
Abdominal Pain/Discomfort [Includes abdominal discomfort, abdominal pain, lower abdominal pain, upper abdominal pain, and abdominal tenderness] | 3 | 2 | 3
Hypertension | 2 | 1 | 0
Headache | 1 | 2 | 2
Electrolyte Abnormalities [Includes increased anion gap, decreased blood bicarbonate, hypomagnesemia, increased blood osmolarity, hypokalemia, hyperkalemia, hypercalcemia, hypernatremia, hyperosmolar state, hyperuricemia, hypocalcemia, and hypophosphatemia] | 1 | 1 | 0
* Reported in at least 1% of patients in either treatment group
N = Total number of patients in the treatment group

Electrolyte Changes

Increases in serum sodium, chloride, calcium, magnesium, phosphate, and urate were noted in more patients treated with PLENVU compared with control in one or both trials. The majority of these changes were transient and not clinically significant. Associated decreases in bicarbonate and increases in serum osmolality were also noted.

Renal Function

Decreases in creatinine clearance and increases in blood urea nitrogen (BUN) were also noted in more patients treated with PLENVU compared to control in both trials. Changes of a magnitude indicative of possible acute renal injury, or worsening of baseline chronic renal impairment, were noted infrequently and occurred at a similar incidence in both PLENVU and comparator arms.

Adverse reactions in patients with mild renal impairment were similar to those in patients with normal renal function.

Less Common Adverse Reactions

Less common adverse reactions (less than 1%) in the NOCT and MORA trials include: anorectal discomfort, hypersensitivity reaction (including rash), migraine, somnolence, asthenia, chills, pains, aches, palpitation, sinus tachycardia, hot flush, and transient increase in liver enzymes.

An additional 235 patients were exposed to the One-Day Morning Dosage Regimen of PLENVU in a third clinical trial, utilizing a comparator not approved in the United States. The adverse reaction profile for patients receiving PLENVU in that trial was similar to what is described above.

6.2 Postmarketing Experience

The following adverse reactions have been identified during post-approval use of another oral formulation of polyethylene glycol 3350, sodium ascorbate, sodium sulfate, ascorbic acid, sodium chloride and potassium chloride or other polyethylene glycol (PEG)-based bowel preparations. Because these reactions are reported voluntarily from a population of uncertain size, it is not always possible to reliably estimate their frequency or establish a causal relationship to drug exposure.

Hypersensitivity: urticaria/rash, pruritus, dermatitis, rhinorrhea dyspnea, chest and throat tightness, fever, angioedema, anaphylaxis and anaphylactic shock [see Contraindications (4)]

Cardiovascular: arrhythmia, atrial fibrillation, peripheral edema, asystole, and acute pulmonary edema after aspiration

Gastrointestinal: upper gastrointestinal bleeding from a Mallory-Weiss tear, esophageal perforation [usually with gastroesophageal reflux disease (GERD)]

Nervous system: tremor, seizure

7 DRUG INTERACTIONS

7.1 Drugs That May Increase Risks Due to Fluid and Electrolyte Abnormalities

Use caution when prescribing PLENVU for patients with conditions and/or who are using medications that increase the risk of fluid and electrolyte disturbances or may increase the risk of renal impairment, seizures, arrhythmias, or QT prolongation in the setting of fluid and electrolyte abnormalities [see Warnings and Precautions (5.1, 5.2, 5.3, 5.4)].

Consider additional patient evaluations as appropriate.

7.2 Potential for Reduced Drug Absorption

PLENVU can reduce the absorption of other coadministered oral drugs. Administer oral medications at least 1 hour before starting each dose of PLENVU [see Dosage and Administration (2.1)].

7.3 Stimulant Laxatives

Concurrent use of stimulant laxatives and PLENVU may increase the risk of mucosal ulceration or ischemic colitis. Avoid use of stimulant laxatives (e.g., bisacodyl, sodium picosulfate) while taking PLENVU [see Warnings and Precautions (5.5)].

8 USE IN SPECIFIC POPULATIONS

8.1 Pregnancy

Risk Summary

There are no available data with PLENVU in pregnant women to inform a drug-associated risk for adverse developmental outcomes. Animal reproduction studies have not been conducted with PLENVU.

The estimated background risk of major birth defects and miscarriage for the indicated population is unknown. All pregnancies have a background risk of birth defect, loss, or other adverse outcomes. In the U.S. general population, the estimated background risk of major birth defects and miscarriage in clinically recognized pregnancies is 2% to 4% and 15% to 20%, respectively.

8.2 Lactation

Risk Summary

There are no data available to assess the presence of PLENVU in human milk, the effects on the breastfed child or the effects on milk production. The lack of clinical data during lactation precludes a clear determination of the risk of PLENVU to a child during lactation; therefore, the developmental and health benefits of breastfeeding should be considered along with the mother’s clinical need for PLENVU and any potential adverse effects on the breastfed child from PLENVU or from the underlying maternal condition.

8.4 Pediatric Use

The safety and effectiveness of PLENVU in pediatric patients has not been established.

8.5 Geriatric Use

Of the approximately 1,000 patients in clinical trials receiving PLENVU, 217 (21%) patients were over 65 years of age. No overall differences in safety or effectiveness were observed between geriatric patients and younger patients, and other reported clinical experience has not identified differences in responses between geriatric patients and younger patients. However, elderly patients are more likely to have decreased hepatic, renal or cardiac function and may be more susceptible to adverse reactions resulting from fluid and electrolyte abnormalities [see Warnings and Precautions (5.1)].

8.6 Renal Impairment

Use PLENVU with caution in patients with renal impairment or patients taking concomitant medications that may affect renal function [see Drug Interactions (7.1)]. These patients may be at risk for renal injury. Advise these patients of the importance of adequate hydration before, during and after the use of PLENVU, and consider performing baseline and post-colonoscopy laboratory tests (electrolytes, creatinine, and BUN) in these patients [see Warnings and Precautions (5.4)].

10 OVERDOSAGE

Overdosage of more than the recommended dose of PLENVU may lead to severe electrolyte disturbances, as well as dehydration and hypovolemia, with signs and symptoms of these disturbances [see Warnings and Precautions (5.1)]. Monitor for fluid and electrolyte disturbances and treat symptomatically.

11 DESCRIPTION

The active ingredients contained in PLENVU are provided in Table 3.

Table 3: Details of Active Ingredients contained in PLENVU
Chemical Name | Chemical Formula | Average Molecular Weight (g/mol) | Chemical Structure
Polyethylene Glycol (PEG) 3350 | H-(OCH2-CH2)n-OH | 3350 | Table 3: Details of Active Ingredients contained in PLENVU
Sodium Ascorbate | C6H7NaO6 | 198.1 | Table 3: Details of Active Ingredients contained in PLENVU
Sodium Sulfate | Na2SO4 | 142.0 | Table 3: Details of Active Ingredients contained in PLENVU
Ascorbic Acid | C6H8O6 | 176.1 | Table 3: Details of Active Ingredients contained in PLENVU
Sodium Chloride | NaCl | 58.4 | Na^+ Cl^-
Potassium Chloride | KCl | 74.6 | K^+ Cl^+

PLENVU (polyethylene glycol 3350, sodium ascorbate, sodium sulfate, ascorbic acid, sodium chloride and potassium chloride for oral solution) is an osmotic laxative consisting of three pouches (one for Dose 1, one for Dose 2 Pouch A and one for Dose 2 Pouch B) containing white to yellow powder for reconstitution.

Dose 1 contains 100 grams of PEG 3350, 9 grams of sodium sulfate, 2 grams of sodium chloride, and 1 gram of potassium chloride, and the following excipients: sucralose, encapsulated citric acid and mango flavoring. When Dose 1 is dissolved in water to a volume of 16 fluid ounces, PLENVU Dose 1 (PEG 3350, sodium sulfate, sodium chloride and potassium chloride) is an oral solution having a mango flavor.

Each Dose 2 Pouch A contains 40 grams of PEG 3350, 3.2 grams of sodium chloride, and 1.2 grams of potassium chloride, and the following excipients: aspartame and fruit punch flavoring.

Each Dose 2 Pouch B contains 48.11 grams of sodium ascorbate and 7.54 grams of ascorbic acid.

When Dose 2 Pouch A and Dose 2 Pouch B are dissolved together in water to a volume of 16 fluid ounces, PLENVU Dose 2 (sodium ascorbate, PEG 3350, ascorbic acid, sodium chloride and potassium chloride) is an oral solution having a fruit punch flavor.

The entire reconstituted 32 fluid ounces of PLENVU bowel preparation contains 140 grams of PEG 3350, 48.11 grams of sodium ascorbate, 9 grams of sodium sulfate, 7.54 grams of ascorbic acid, 5.2 grams of sodium chloride and 2.2 grams of potassium chloride and the following excipients: aspartame, sucralose, encapsulated citric acid, mango and fruit punch flavorings.

A mixing container for reconstitution is enclosed.

Phenylketonurics: Contains Phenylalanine 491 mg per treatment.

Contains no ingredient made from a gluten-containing grain (wheat, barley, or rye).

12 CLINICAL PHARMACOLOGY

12.1 Mechanism of Action

The primary mode of action is osmotic action of the components of PLENVU (PEG 3350 plus sodium sulfate components in Dose 1, and sodium ascorbate and ascorbic acid plus PEG 3350 components in Dose 2) which induce the laxative effect. The physiological consequence is increased water retention in the lumen of the colon, resulting in loose stools.

12.2 Pharmacodynamics

The osmotic effect of the unabsorbed PEG, ascorbate and sulfate ions, when ingested, produces a copious watery diarrhea.

The first bowel movement may happen about 1 to 2 hours after the start of PLENVU intake.

12.3 Pharmacokinetics

The plasma pharmacokinetic parameters for PEG 3350, ascorbate and sulfate are shown in Table 4.

Table 4: Plasma Pharmacokinetic Data Following Two-Day Split Dosage Regimen of 140 grams PEG 3350, 33.9 grams Sodium Ascorbate, 9 grams Sodium Sulfate, 20.1 grams Ascorbic Acid, 4.8 grams Sodium Chloride and 2.3 grams Potassium Chloride in Healthy Subjects [Four-day study with controlled diet including fasting from 2 pm on Day 1 to 2 pm on Day 2.] (N=21) [Product studied contains the same amount of PEG 3350 and sodium sulfate, although the amount of sodium ascorbate and ascorbic acid are slightly different, compared to PLENVU.]
PK Parameter | PEG 3350 Mean (SD) | Ascorbate [Baseline-corrected] Mean (SD) | Sulfate Mean (SD)
Cmax [mcg/mL] | 2.7 (1.17) | 70.8 (22.37) | 17.6 (4.80)
Tmax [h] | 3.0 (0.61) | 16.8 (0.75) | 8.1 (5.51)
AUC(0-tlast) [mcg●h/mL] | 17.3 (7.19) | 433.1 (157.29) | 206.2 (74.32)
Vd [l] | 48,481 (29,811) | 1,026 (675) | 231 (205)
t1/2 [h] | 4.1 (2.34) | 7.2 (6.16) | 10.5 (15.19)

SD = standard deviation; Cmax = maximum concentration; Tmax = time to maximum concentration from start of dosing; AUC(0-tlast) = area under the curve from t0 to tlast; Vd = volume of distribution; t1/2 = half-life.

A pharmacokinetic study measured up to 85% to 99% of a 140 grams oral PEG 3350 dose in excreted feces.

A pharmacokinetic study measured up to 69% of a 50 grams oral ascorbate dose in excreted feces and up to 5% of the 50 grams oral ascorbate dose is recovered in the urine (with up to 0.07% as the ascorbate metabolite, oxalic acid).

Sulfate is endogenous and also present in the diet. A pharmacokinetic study measured up to 69% to 73% of a 9 grams oral sodium sulfate dose in excreted feces, with approximately 43% recovered in the urine.

Following a One-Day Morning Dosage regimen of PLENVU, Cmax values of glycolic acid (after baseline correction) ranged from 76 to 1,770 ng/mL with a median Tmax of 9 hours and AUC0-last in the range of 3,770 to 17,700 ng●h/mL. The concentrations of ethylene glycol and diethylene glycol in any individual subject were lower than 2.5 mcg/mL (lower limit of quantitation (LLOQ): 2.5 mcg/mL) and oxalic acid was not measurable (LLOQ: 10 mcg/mL).

14 CLINICAL STUDIES

Study Design

The colon cleansing efficacy, safety and tolerability of PLENVU was evaluated in two randomized, parallel-group, multicenter, investigator-blinded trials in adult patients scheduled to undergo a screening, surveillance, or diagnostic colonoscopy. The overall patient population consisted of 49% male and 51% female patients, mean age of 56 years (range 18 to 86 years), 92% Caucasian, 5% Black and 2% Asian. In general, the demographic characteristics were balanced across the trials.

In Study NER1006-01/2014 (referred to as NOCT; NCT02254486) and Study NER1006-02/2014 (referred to as MORA; NCT02273167), the bowel cleansing efficacy of PLENVU was compared to two different comparators (see Table 5) using two different PLENVU dosing regimen(s):

- PLENVU Two-Day Split Dosage regimen allows for an overnight gap between doses (Dose 1 taken in the evening before the colonoscopy, between approximately 4 pm and 8 pm, and Dose 2 the next morning, on the day of the colonoscopy, approximately 12 hours after the start of Dose 1).
- PLENVU One-Day Morning Dosage regimen gives both doses the morning of the day of colonoscopy (Dose 1 between approximately 3 am and 7 am, and Dose 2 a minimum of 2 hours after the start of Dose 1).

Table 5: Treatment Regimens by Trial
Trial | PLENVU Dosage Regimen(s) | Comparator Regimens
NOCT | Two-Day Split Dosage | Trisulfate bowel cleansing solution administered as a Two-Day Split Dosage regimen:; - [Trisulfate (Two 6-ounce bottles each containing sodium sulfate 17.5 grams, potassium sulfate 3.13 grams, and magnesium sulfate 1.6 grams)]
MORA | Two-Day Split Dosage and One-Day Morning Dosage | 2 liter PEG + electrolytes (2 L PEG+E) preparation administered as a Two-Day Split Dosage regimen:; - Two doses, each containing PEG 3350 100 grams, sodium sulfate 7.5 grams, sodium chloride 2.691 grams, potassium chloride 1.015 grams, sodium ascorbate 5.9 grams, and ascorbic acid 4.7 grams

Primary Endpoint

The primary efficacy endpoint in both trials was the proportion of patients achieving “overall bowel cleansing success,” which was defined by a result of Grade A or B (Grades A or B [see Table 6] corresponding to full visualization of the bowel mucosa on the Harefield Cleansing Scale [HCS]), as assessed on withdrawal of colonoscope. The HCS segmental scores were initially evaluated by the colonoscopist at the site, who was blinded to treatment, and evaluated for endpoint analysis by central readers (gastroenterologists) using video recordings of the colonoscopy.

Table 6: Harefield Cleansing Scale
Overall Grade | Description
A | All five segments* scored 3 or 4 (Mucosa is fully visualized without cleaning.)
B | One or more segments scored 2, remaining segments scored 3 or 4 (Mucosa is fully visualized.)
C | One or more segments scored 1, remaining segments scored 2, 3 or 4
D | One or more segments scored 0
Segmental Score | Description
4 | Empty and clean
3 | Clear liquid
2 | Brown liquid/fully removable semisolid stools
1 | Semisolid, only partially removable stools
0 | Irremovable, heavy, hard stools
* Colon ascendens, Colon transversum, Colon descendens, Colon sigmoideum, Rectum

Statistical Analysis
The modified Intent-to-Treat (mITT) population was used as the primary population for the efficacy analyses and was defined as all randomized patients with the exception of any patient who (i) was randomized but subsequently failed to meet entry criteria and (ii) in whom it was confirmed (from their patient diary) that the same patient did not receive any study drug.

Non-inferiority was assessed using a one-sided 97.5% confidence interval (CI) for the difference in proportions of patients for the overall bowel cleansing success endpoint. Non-inferiority was demonstrated if the difference between PLENVU and the comparator was above the predefined non-inferiority margin set at -10%.

Efficacy Results
The results for the overall bowel cleansing success endpoint in the mITT population in NOCT are shown in Table 7. The Two-Day Split Dosage regimen of PLENVU was shown to be non-inferior (NI) to the trisulfate solution comparator.

Table 7: Overall Bowel Cleansing Success Rate of PLENVU versus Trisulfate in NOCT
Primary Endpoint; (N=556) | PLENVU; Two-Day; Split Dosage Regimen; (N=276); n (% = n/N*100) | Trisulfate; Two-Day; Split Dosage Regimen; (N=280); n (% = n/N*100) | PLENVU® - Trisulfate Difference (%); (97.5% One-Sided Lower; Confidence Interval)
Overall Colon; Cleansing Success; Rate | 235; (85.1%) | 238; (85.0%) | 0.1%; (-8.2%)

The results for the overall bowel cleansing success endpoint in the mITT population in MORA are shown in Table 8. Both the PLENVU Two-Day Split Dosage regimen and the PLENVU One-Day Morning Dosage regimen were shown to be non-inferior (NI) to the 2 L PEG+E treatment comparator.

Table 8: Overall Bowel Cleansing Success Rate of PLENVU versus 2 L PEG+E in MORA
Primary Endpoint (N=822) | PLENVU Two-Day Split Dosage Regimen (N=275) n (% = n/N*100) | PLENVU One-Day Morning Dosage Regimen (N=275) n (% = n/N*100) | 2 L PEG+E Two-Day Split Dosage Regimen (N=272) n (% = n/N*100) | PLENVU® Regimen - 2 L PEG+E Difference (%) (97.5% One-Sided Lower Confidence Interval)
Overall Colon Cleansing Success Rate | 253 (92.0%) | 245 (89.1%) | 238 (87.5%) | Two-Day Split Dosage
Overall Colon Cleansing Success Rate | 253 (92.0%) | 245 (89.1%) | 238 (87.5%) | 4.5% (-4.0%)
Overall Colon Cleansing Success Rate | 253 (92.0%) | 245 (89.1%) | 238 (87.5%) | One-Day Morning Dosage
Overall Colon Cleansing Success Rate | 253 (92.0%) | 245 (89.1%) | 238 (87.5%) | 1.6% (-6.9%)

16 HOW SUPPLIED/STORAGE AND HANDLING

PLENVU (polyethylene glycol 3350, sodium ascorbate, sodium sulfate, ascorbic acid, sodium chloride and potassium chloride for oral solution) is supplied as a white to yellow powder for reconstitution.

Dose 1 contains 100 grams of PEG 3350, 9 grams of sodium sulfate, 2 grams of sodium chloride, and 1 gram of potassium chloride: NDC 65649-400-01.

Dose 2 Pouch A contains 40 grams of PEG 3350, 3.2 grams of sodium chloride, and 1.2 grams of potassium chloride: NDC 65649-400-01.

Dose 2 Pouch B contains 48.11 grams of sodium ascorbate and 7.54 grams of ascorbic acid: NDC 65649-400-01.

PLENVU, single-use inner carton: The inner carton contains three pouches labeled Dose 1, Dose 2 Pouch A and Dose 2 Pouch B: NDC 65649-400-01.

PLENVU, single-use outer carton: Each outer carton contains the inner carton, prescribing information and patient information and a disposable mixing container with lid for reconstitution of PLENVU: NDC 65649-400-01.

Storage

Store pack at room temperature, between 68°F to 77°F (20°C to 25°C) with excursions permitted to 59°F to 86°F (15°C to 30°C) [see USP Controlled Room Temperature]. The pack may be stored in a refrigerator.

17 PATIENT COUNSELING INFORMATION

Advise the patient to read the FDA-approved patient labeling (Medication Guide and Instructions for Use).

Instruct patients:

- Two doses of PLENVU are required for a complete preparation for colonoscopy either as a Two-Day Split Dosage or One-Day Morning Dosage regimen [see Instructions for Use].
- Follow the directions in the Instructions for Use, for either the Two-Day Split Dosage or the One-Day Morning Dosage regimen, as prescribed.
- Reconstitute each pouch of PLENVU in the mixing container with water before ingestion and drink additional clear liquids. Examples of clear liquids can be found in the Instructions for Use. Do not reconstitute with other liquids and/or add starch-based thickeners to the mixing container [see Warnings and Precautions (5.7)].
- Consume additional clear liquids before, during, and after the use of PLENVU to prevent dehydration [see Warnings and Precautions (5.1)].
- Consume only clear liquids (no solid food) from the start of PLENVU treatment until after the colonoscopy.
- Do not eat or drink alcohol, milk, anything colored red or purple or any other foods containing pulp material.
- Do not take other laxatives while taking PLENVU.
- PLENVU contains 491 mg of phenylalanine per treatment [see Warnings and Precautions (5.9)].
- Administer oral medications at least 1 hour before starting each dose of PLENVU.
- Contact their healthcare provider if they develop significant vomiting or signs of dehydration after taking PLENVU or if they experience altered consciousness or seizures [see Warnings and Precautions (5.1, 5.2, 5.3, 5.4)].
- Stop drinking PLENVU temporarily or drink each portion at longer intervals if severe abdominal discomfort or distention develops until these symptoms diminish. If severe symptoms persist, contact their healthcare provider.

Distributed by:
Salix Pharmaceuticals, a division of
Bausch Health US, LLC
Bridgewater, NJ 08807 USA

Manufactured by:
Norgine Limited
7 Tir-y-berth Industrial Estate
New Road, Tir-y-berth
Hengoed, CF82 8SJ
United Kingdom (GBR)

Patented. See https://patents.salix.com for US patent information.

PLENVU is a registered trademark of the Norgine group of companies used under license.

© 2023 Salix Pharmaceuticals, Inc. or its affiliates

9643003

Medication Guide

PLENVU® (plen-vu)
(polyethylene glycol 3350, sodium ascorbate, sodium sulfate, ascorbic acid, sodium chloride
and potassium chloride for oral solution)

Read this Medication Guide and Instructions for Use before your colonoscopy and again before you start taking PLENVU.

What is the most important information I should know about PLENVU?

PLENVU and other bowel preparations can cause serious side effects, including:

- Serious loss of body fluid (dehydration) and changes in blood salts (electrolytes) in your blood. These changes can cause:
  - abnormal heartbeats that can cause death.
  - seizures. This can happen even if you have never had a seizure.
  - kidney problems.

Your chance of having fluid loss and changes in body salts with PLENVU is higher if you:

  - have heart problems.
  - have kidney problems.
  - take water pills (diuretics), high blood pressure medicine or non-steroidal anti-inflammatory drugs (NSAIDs).

Tell your healthcare provider right away if you have any of these symptoms of serious loss of body fluid (dehydration) while taking PLENVU:

- vomiting
- dizziness

- urinating less often than normal
- headache

See “What are the possible side effects of PLENVU?” for more information about side effects.

What is PLENVU?
PLENVU is a prescription medicine used by adults to clean the colon before a colonoscopy. PLENVU cleans your colon by causing you to have diarrhea (loose stools). Cleaning your colon helps your healthcare provider see the inside of your colon more clearly during your colonoscopy.
It is not known if PLENVU is safe and effective in children.

Do not take PLENVU if your healthcare provider has told you that you have:

- a blockage in your intestine (bowel obstruction).
- an opening in the wall of your stomach or intestine (bowel perforation).
- problems with food and fluid emptying from your stomach (gastric retention).
- a problem with food moving too slowly through your intestines (ileus).
- a very dilated intestine (toxic megacolon).
- an allergy to any of the ingredients in PLENVU. See the end of this Medication Guide for a complete list of ingredients in PLENVU.

Before taking PLENVU, tell your healthcare provider about all of your medical conditions, including if you:

- have problems with serious loss of body fluid (dehydration) and changes in blood salts (electrolytes).
- have heart problems.
- have seizures or take medicines for seizures.
- have kidney problems or take medicines for kidney problems.
- have stomach or bowel problems, including ulcerative colitis.
- have problems with swallowing, gastric reflux or if you inhale food or fluid into your lungs when eating or drinking (aspirate).
- have a condition called glucose-6-phosphate dehydrogenase (G6PD) deficiency that destroys red blood cells.
- are withdrawing from drinking alcohol.
- have phenylketonuria (PKU). PLENVU contains phenylalanine.
- are allergic to any of the ingredients in PLENVU.
- are pregnant or plan to become pregnant. It is not known if PLENVU will harm your unborn baby. Talk to your healthcare provider if you are pregnant.
- are breastfeeding or plan to breastfeed. It is not known if PLENVU passes into your breast milk. You and your healthcare provider should decide if you will take PLENVU while breastfeeding.

Tell your healthcare provider about all the medicines you take, including prescription and over-the-counter medicines, vitamins, and herbal supplements.

PLENVU may affect how other medicines work. If you need to take any other medicines by mouth, take those medicines at least 1 hour before starting each dose of PLENVU.

Especially tell your healthcare provider if you take:

- medicines to treat a blood salt (electrolyte) imbalance.
- medicines for blood pressure or heart problems.
- medicines for seizures (antiepileptics).
- medicines for kidney problems.
- water pills (diuretics).
- non-steroidal anti-inflammatory drugs (NSAIDs).
- laxatives. Do not take other laxatives while taking PLENVU.
- medicines for depression or other mental health problems.
- starch based thickeners. For patients who have trouble swallowing, do not mix PLENVU with starch-based thickeners

Ask your healthcare provider or pharmacist for a list of these medicines if you are not sure if you are taking any of the medicines listed above.

Know the medicines you take. Keep a list of them to show your healthcare provider and pharmacist when you get a new medicine.

How should I take PLENVU?

See the Instructions for Use for dosing instructions. You must read, understand, and follow these instructions to take PLENVU the right way.

- Take PLENVU exactly as your healthcare provider tells you to take it. Your healthcare provider will tell you to take the Two-Day Split Dosage option or the One-Day Morning Dosage option.
- Drink clear liquids before, during, and after you take PLENVU, up until 2 hours before your colonoscopy, to help prevent fluid loss (dehydration) and changes in blood salt (electrolyte) levels.
- Do not eat solid food while taking PLENVU until after your colonoscopy.
- It is important for you to drink the additional amount of clear liquids listed in the Instructions for Use.
- You may have stomach-area (abdomen) bloating after your first dose of PLENVU.
  - If you have severe stomach-area (abdomen) discomfort or bloating, stop drinking PLENVU for a short time or wait a longer time between each dose of PLENVU until your stomach-area symptoms improve. If your stomach‑area discomfort or bloating continues, tell your healthcare provider.
- Your first bowel movement may happen about 1 to 2 hours after you start taking PLENVU.
- If you take too much PLENVU, call your healthcare provider.

What are the possible side effects of PLENVU?

PLENVU can cause serious side effects including:

- Changes in certain blood tests. Your healthcare provider may do blood tests after you take PLENVU to check your blood for changes. Tell your healthcare provider if you have any symptoms of too much fluid loss, including:

- vomiting
- dizziness

- heart problems
- kidney problems

- seizures
- dry mouth

- feel faint, weak or lightheaded especially when you stand up (orthostatic hypotension)

- Ulcers of the bowel or bowel problems (ischemic colitis): Tell your healthcare provider right away if you have severe stomach-area (abdomen) pain or rectal bleeding.
- Serious allergic reactions. Symptoms of a serious allergic reaction may include:

- skin rash
- itching

- raised red patches on your skin (hives)
- swelling of the face, lips, tongue and throat

- kidney problems

The most common side effects of PLENVU include:

- nausea

- vomiting

- dehydration

- stomach pain or discomfort

These are not all the possible side effects of PLENVU.

Call your doctor for medical advice about side effects. You may report side effects to FDA at 1-800-FDA-1088.

How should I store PLENVU?

- Store PLENVU (before opening and after mixed) at room temperature, between 68°F to 77°F
  (20°C to 25°C). PLENVU (before opening and after mixed) may also be stored in a refrigerator.
- Use PLENVU within 24 hours after mixing with water.

Keep PLENVU and all medicines out of the reach of children.

General information about the safe and effective use of PLENVU.

Medicines are sometimes prescribed for purposes other than those listed in a Medication Guide. Do not use PLENVU for a condition for which it was not prescribed. Do not give PLENVU to other people, even if they are going to have the same procedure you are. It may harm them.

You can ask your pharmacist or healthcare provider for information that is written for health professionals.

What are the ingredients in PLENVU?

Active ingredient:

Dose 1: PEG 3350, sodium sulfate, sodium chloride, potassium chloride

Dose 2 Pouch A: PEG 3350, sodium chloride, potassium chloride

Dose 2 Pouch B: sodium ascorbate, ascorbic acid

Inactive ingredients:

Dose 1: sucralose, encapsulated citric acid, mango flavoring

Dose 2 Pouch A: aspartame, fruit punch flavoring

Distributed by:

Salix Pharmaceuticals, a division of

Bausch Health US, LLC

Bridgewater, NJ 08807 USA
Manufactured by:

Norgine Limited

7 Tir-y-berth Industrial Estate

New Road, Tir-y-berth

Hengoed, CF82 8SJ

United Kingdom (GBR)

Patented. See https://patents.salix.com for US patent information.

PLENVU is a registered trademark of the Norgine group of companies used under license.

© 2023 Salix Pharmaceuticals, Inc. or its affiliates

For more information, go to www.PLENVU.com or call 1-800-321-4576.

This Medication Guide has been approved by the U.S. Food and Drug Administration.

Revised: 9/2023 9643003

Instructions for Use

PLENVU® (plen-vu)

(polyethylene glycol 3350, sodium ascorbate, sodium sulfate, ascorbic acid, sodium chloride and potassium chloride for oral solution)

There are two different options for taking PLENVU. Your healthcare provider will tell you to take the Two-Day Split-Dosage option or the One-Day Morning Dosage option.

The following are provided with the pack:

- An outer carton:

- An inner carton:

- A mixing container
  with removable lid:

- Prescribing Information
  and Patient Information

The inner carton contains:

- Dose 1

- Dose 2 Pouch A and Dose 2
  Pouch B (to be taken together)

Additional supplies (not included in the pack):

- Water (to mix with PLENVU).
- Scissors (optional to cut the pouches on the dotted line).
- Spoon (optional to mix the water and PLENVU together. You can also mix the water and PLENVU by putting the lid on securely and shaking it. See step 1c below).

Important Information on PLENVU:

- You must drink all of Dose 1 (one pouch) and Dose 2 (two pouches) of PLENVU for either dosing option. Make sure you finish Dose 2 at least 2 hours before your colonoscopy. Do not add any other ingredients to PLENVU.
- Do not mix PLENVU with starch-based thickeners.
- PLENVU must be mixed with water.
- Drink clear liquids before, during, and after you take PLENVU, up until 2 hours before your colonoscopy, to help prevent fluid loss (dehydration), and changes in blood salt (electrolyte) levels.

It is important for you to drink the additional amount of clear liquids listed here in the Instructions for Use.

Examples of clear liquids are:

  - water
  - clear broth soups
  - herbal tea, black tea or coffee
  - watered down (diluted) (from concentrate) clear fruit juices (without pulp) including apple juice or white grape juice
  - clear soda
  - gelatin (without added fruit or topping)
  - popsicles (without pieces of fruit or fruit pulp)
  - strained limeade or lemonade
- Do not eat or drink alcohol, milk, anything colored red or purple or any foods that have pulp.
- Do not take other laxatives while taking PLENVU.
- If you need to take any other medicines by mouth (oral), take those medicines at least 1 hour before starting each dose of PLENVU.
- Do not eat solid food while taking PLENVU until after your colonoscopy.
- For the Two-Day Split Dosage schedule:
  - On the day before the colonoscopy you can eat a light breakfast followed by a light lunch.
  - You must finish eating lunch at least 3 hours before you start taking PLENVU.
  - After you start taking PLENVU you can only drink clear liquids.
- For the One-Day Morning Dosage schedule:
  - On the day before the colonoscopy you can eat a light breakfast followed by a light lunch. For dinner you may have clear broth soup or plain yogurt.
  - You should finish dinner by about 8 pm.
  - After you start taking PLENVU you can only drink clear liquids.
- Do not eat the morning of your colonoscopy.

Two-Day Split Dosage Schedule

Take Dose 1 in the evening sometime between 4 pm and 8 pm.

Take Dose 2 the next morning, on the day of the colonoscopy. This should be about 12 hours (between about 4 am and 8 am) after you started Dose 1. Make sure you finish Dose 2 at least 2 hours before your colonoscopy.

Follow Step 1 to Step 3 on how to mix with a spoon or shake with lid on securely and take PLENVU:

Step 1a: Empty Dose 1 into the mixing container that comes with your PLENVU.

Step 1b: Add water to the fill line. You will need to add at least 16 ounces.

Step 1c: Mix the water and PLENVU together with a spoon or put lid on mixing container securely and shake the water and PLENVU, until it is completely dissolved. This can take 2 to 3 minutes.

Step 2: Drink the entire contents of the mixing container over the next 30 minutes.
If you feel like you have severe stomach pain or discomfort you can stop taking PLENVU for a short time and then continue taking it or you can take smaller sips of PLENVU so that you space out your dose longer than 30 minutes. If you still have severe stomach pain, call your healthcare provider.

Step 3: Rinse the mixing container with water. Refill to the fill line with clear liquids. This will be at least 16 ounces. Drink the entire contents of the mixing container over the next 30 minutes. Continue to drink additional clear liquids during the evening as this is important to help avoid dehydration. For a list of clear liquids, see examples at the top of the Instructions for Use.

After taking PLENVU if you have any bloating or feeling like your stomach is upset, wait to take Dose 2 until your stomach feels better.
  For Dose 2: Rinse the mixing container with water. Repeat Steps 1, 2 and 3 but this time for Dose 2 you will empty two dose pouches (Dose 2 Pouch A and Dose 2 Pouch B) into the mixing container at the same time.
  After drinking your 16 ounces of water mixed with PLENVU and the 16 ounces of the clear liquids, it is important that you drink additional clear liquids to help avoid dehydration. For a list of clear liquids, see examples at the top of the Instructions for Use. You must stop drinking all liquids at least 2 hours before your colonoscopy.

One-Day Morning Dosage Schedule

Take Dose 1 the morning of your colonoscopy sometime between 3 am and 7 am.

Take Dose 2 about two hours after you start Dose 1. Make sure you finish Dose 2 at least 2 hours before your colonoscopy.

Follow Step 1, Step 2 and Step 3 on how to mix with a spoon or shake with lid on securely and take PLENVU:

Step 1a: Empty Dose 1 into the mixing container that comes with your PLENVU.

Step 1b: Add water to the fill line. You will need to add at least 16 ounces.

Step 1c: Mix the water and PLENVU together with a spoon or put lid on mixing container securely and shake the water and PLENVU, until it is completely dissolved. This can take 2 to 3 minutes.

Step 2: Drink the entire contents of the mixing container over the next 30 minutes.
If you feel like you have severe stomach pain or discomfort you can stop taking PLENVU for a short time and then continue taking it or you can take smaller sips of PLENVU so that you space out your dose longer than 30 minutes. If you still have severe stomach pain, call your healthcare provider.

Step 3: Rinse the mixing container with water. Refill to fill line with clear liquids. This will be at least 16 ounces. Drink the entire contents of the mixing container over the next 30 minutes.
  After drinking your 16 ounces of water mixed with PLENVU and the 16 ounces of the clear liquids, it is important that you drink additional clear liquids in the morning before Dose 2 to help avoid dehydration. For a list of clear liquids, see examples at the top of the Instructions for Use. You must stop drinking all liquids at least 2 hours before your colonoscopy.

After taking PLENVU if you have any bloating or feeling like your stomach is upset, wait to take Dose 2 until your stomach feels better.
  For Dose 2: Rinse the mixing container with water. Repeat Step 1, Step 2 and Step 3 but this time for Dose 2 you will empty two dose pouches (Dose 2 Pouch A and Dose 2 Pouch B) into the mixing container at the same time.
  After drinking your 16 ounces of water mixed with PLENVU and the 16 ounces of the clear liquids, it is important that you drink additional clear liquids to help avoid dehydration. For a list of clear liquids, see examples at the top of the Instructions for Use. You must stop drinking all liquids at least 2 hours before your colonoscopy.

Distributed by:
Salix Pharmaceuticals, a division of
Bausch Health US, LLC
Bridgewater, NJ 08807 USA

Manufactured by:
Norgine Limited
7 Tir-y-berth Industrial Estate
New Road, Tir-y-berth
Hengoed, CF82 8SJ
United Kingdom (GBR)

Patented. See https://patents.salix.com for US patent information.

PLENVU is a registered trademark of the Norgine group of companies used under license.
© 2023 Salix Pharmaceuticals, Inc. or its affiliates
This Instructions for Use has been approved by the U.S. Food and Drug Administration.
Revised: 9/2023

9643003

PACKAGE/LABEL PRINCIPAL DISPLAY PANEL – Plenvu Outer Carton

Rx only
NDC 65649-400-01
PLENVU®

(polyethylene glycol 3350, sodium ascorbate,
sodium sulfate, ascorbic acid, sodium chloride
and potassium chloride for oral solution)
140 g, 48.11 g, 9 g, 7.54 g, 5.2 g, 2.2 g

This carton contains:

- Dose 1
- Dose 2 Pouch A
  and Dose 2 Pouch B
- Mixing container with
  fill line
- Prescribing Information
  and patient information

Dose 1 Pouch contains
115.96 g of powder for
oral solution.

Dose 2 Pouch A contains
46.26 g of powder for
oral solution.

Dose 2 Pouch B contains
55.65 g of powder for
oral solution.

All of Dose 1 (one pouch) and Dose 2
(two pouches) must be consumed.

Follow the instructions provided prior
to use.

Phenylketonurics: Contains Phenylalanine
491 mg per treatment.

Dispense the enclosed Medication Guide
to each patient.

Reconstitute and dilute in water prior
to use.

Salix
PHARMACEUTICALS

9642903